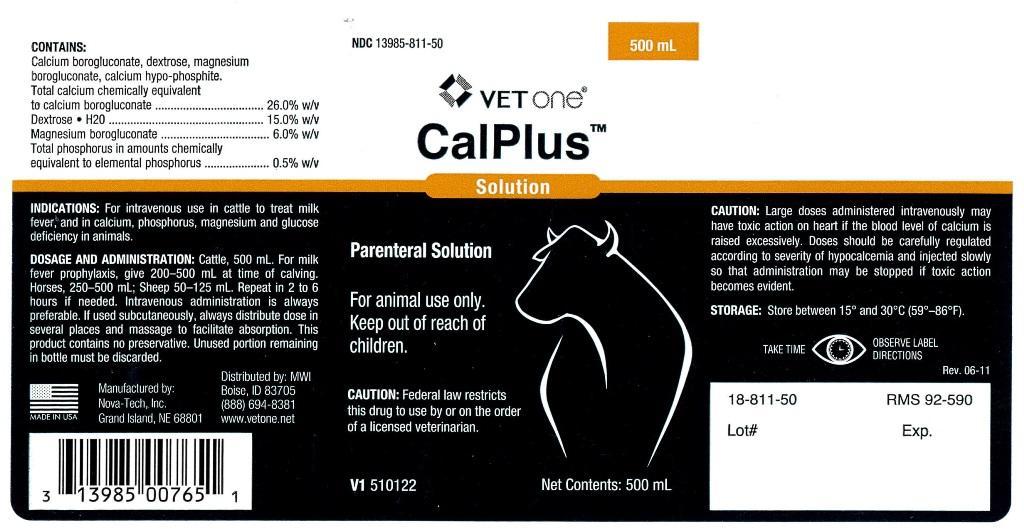 DRUG LABEL: CalPlus
NDC: 13985-811 | Form: INJECTION, SOLUTION
Manufacturer: MWI (VetOne)
Category: animal | Type: PRESCRIPTION ANIMAL DRUG LABEL
Date: 20250909

ACTIVE INGREDIENTS: Calcium Borogluconate 26 g/100 mL; DEXTROSE MONOHYDRATE 15 g/100 mL; Magnesium Gluconate 6 g/100 mL; Phosphorus 0.5 g/100 mL

CalPlus

CONTAINS:

Calcium borogluconate, dextrose, magnesium
borogluconate, calcium hypo-phosphite.
Total calcium chemically equivalent
to calcium borogluconate .................................... 26.0% w/v
Dextrose H20 .................................................... 15.0% w/v
Magnesium borogluconate .................................... 6.0% w/v
Total phosphorus in amounts chemically
equivalent to elemental phosphorus ....................... 0.5% w/v

INDICATIONS:

For intravenous use in cattle to treat milk
fever, and in calcium, phosphorus, magnesium and glucose
deficiency in animals.

DOSAGE AND ADMINISTRATION:

Cattle, 500 mL. For milk
fever prophylaxis, give 200-500 mL at time of calving.
Horses, 250-500 mL; Sheep 50-125 mL. Repeat in 2 to 6
hours if needed. Intravenous administration is always
preferable. If used subcutaneously, always distribute dose in
several places and massage to facilitate absorption. This
product contains no preservative. Unused portion remaining
in bottle must be discarded.

GENERAL PRECAUTIONS

Parental Solution

For animal use only.

Keep out of reach of children.

CAUTION:

Federal law restricts this drug to use by or on the order of a licensed veterinarian.

CAUTION:

Large doses administered intravenously may
have toxic action on heart if the blood level of calcium is
raised excessively. Doses should be carefully regulated
according to severity of hypocalcemia and injected slowly
so that administration may be stopped if toxic action
becomes evident.

STORAGE:

Store between 15 degrees and 30 degrees C (59 degrees - 86 degrees F).

GENERAL PRECAUTIONS

TAKE TIME OBSERVE LABEL DIRECTIONS

INFORMATION FOR OWNERS/CAREGIVERS

Manufactured by:
Nova-Tech, Inc.
Grand Island, NE 68801

Distributed by: MWI
Boise, ID 83705
(888) 694-8381
www.vetone.net

V1 510122 Net Contents: 500 mL

Rev. 06-11

18-811-50 RMS 92-590

Lot# Exp.